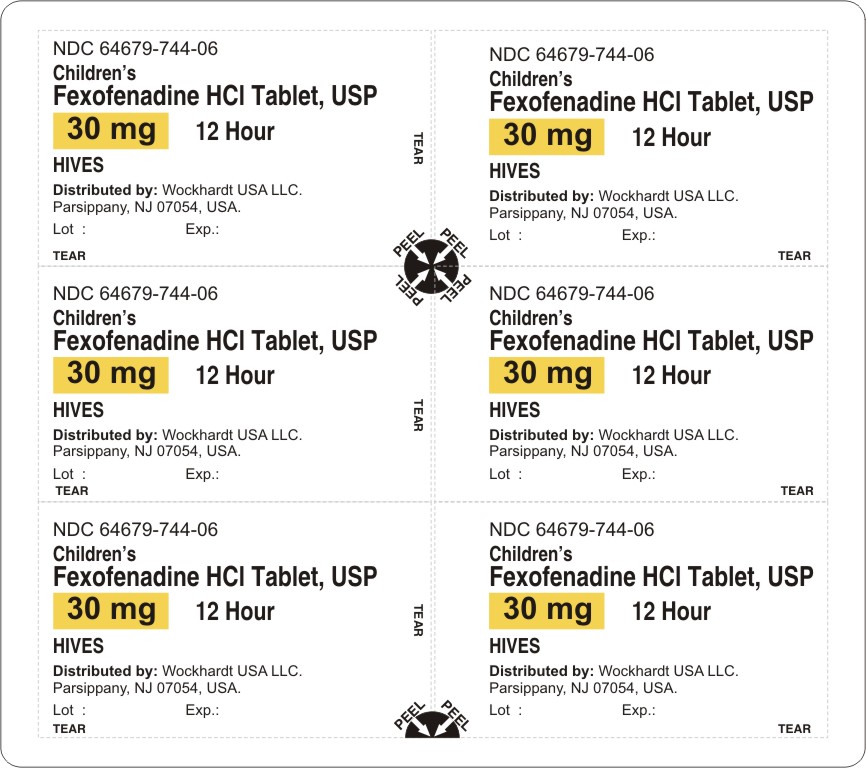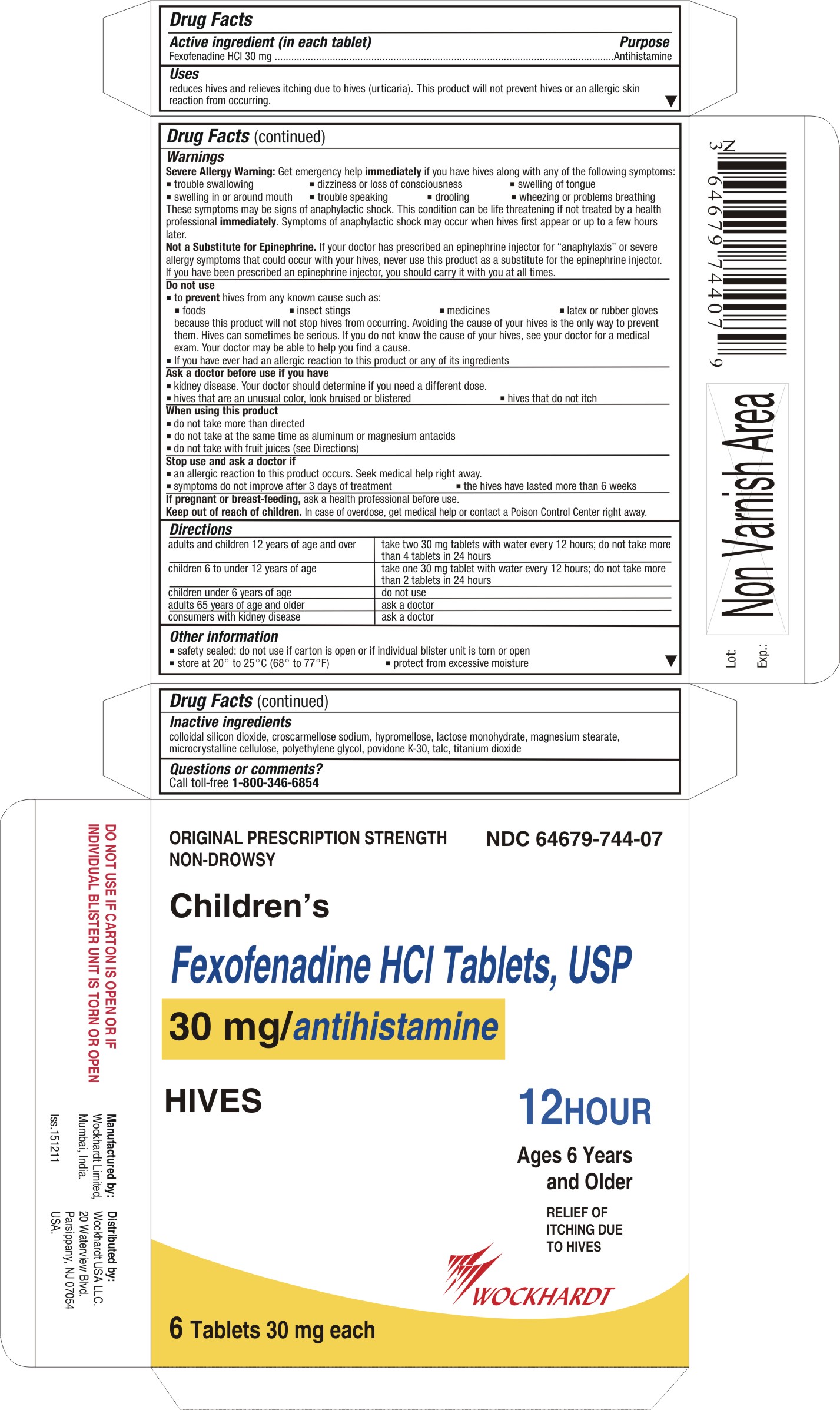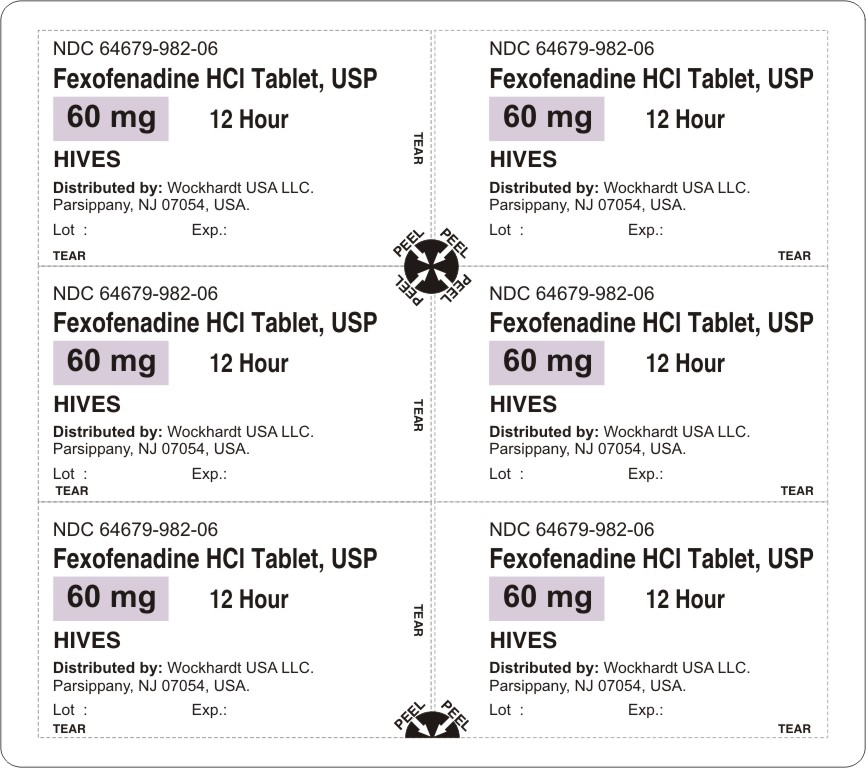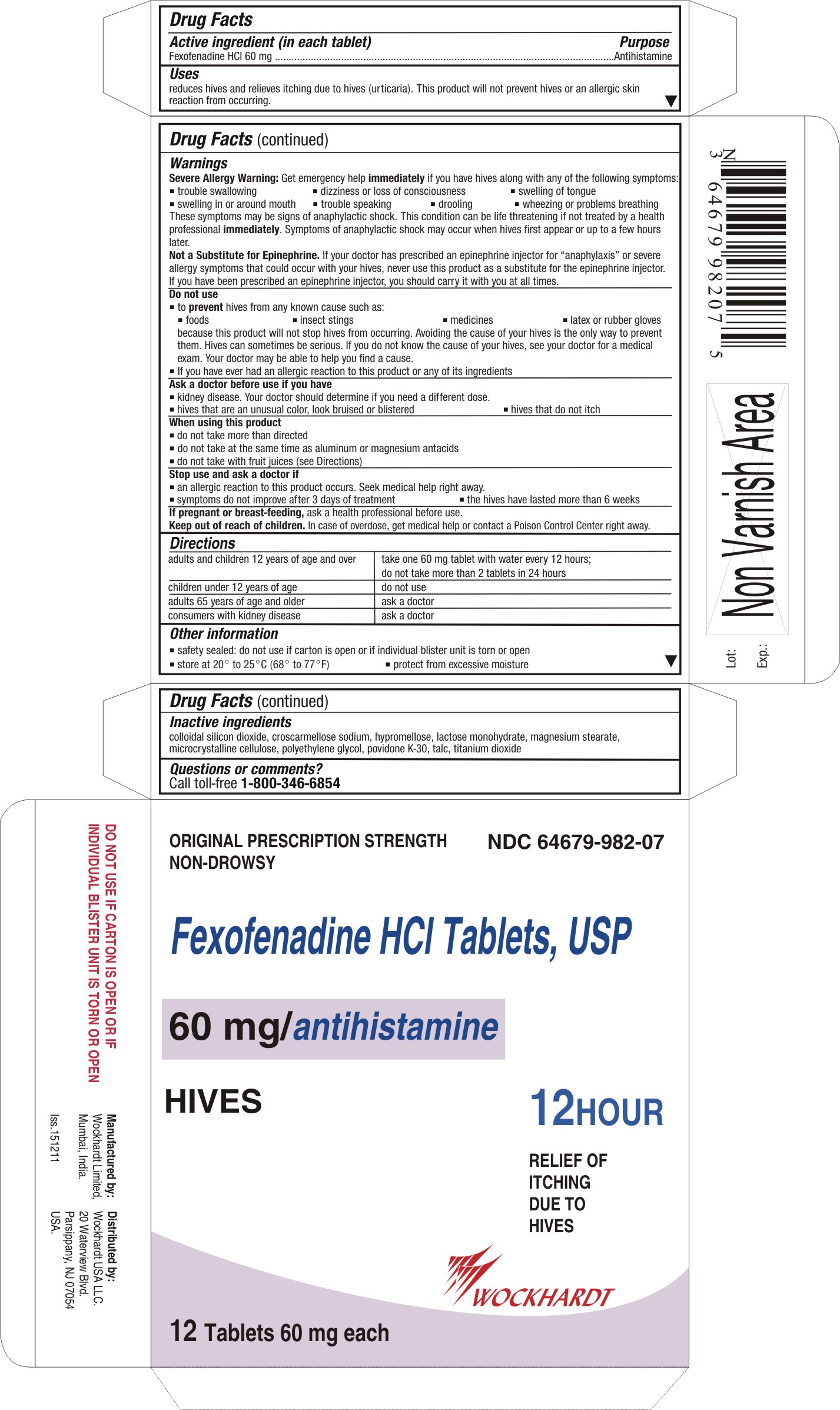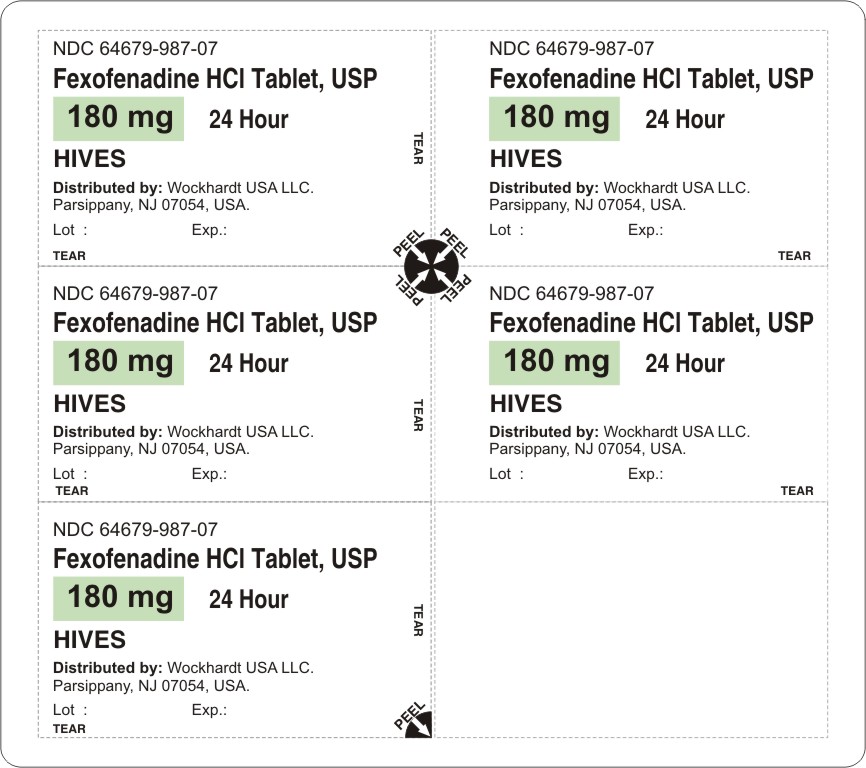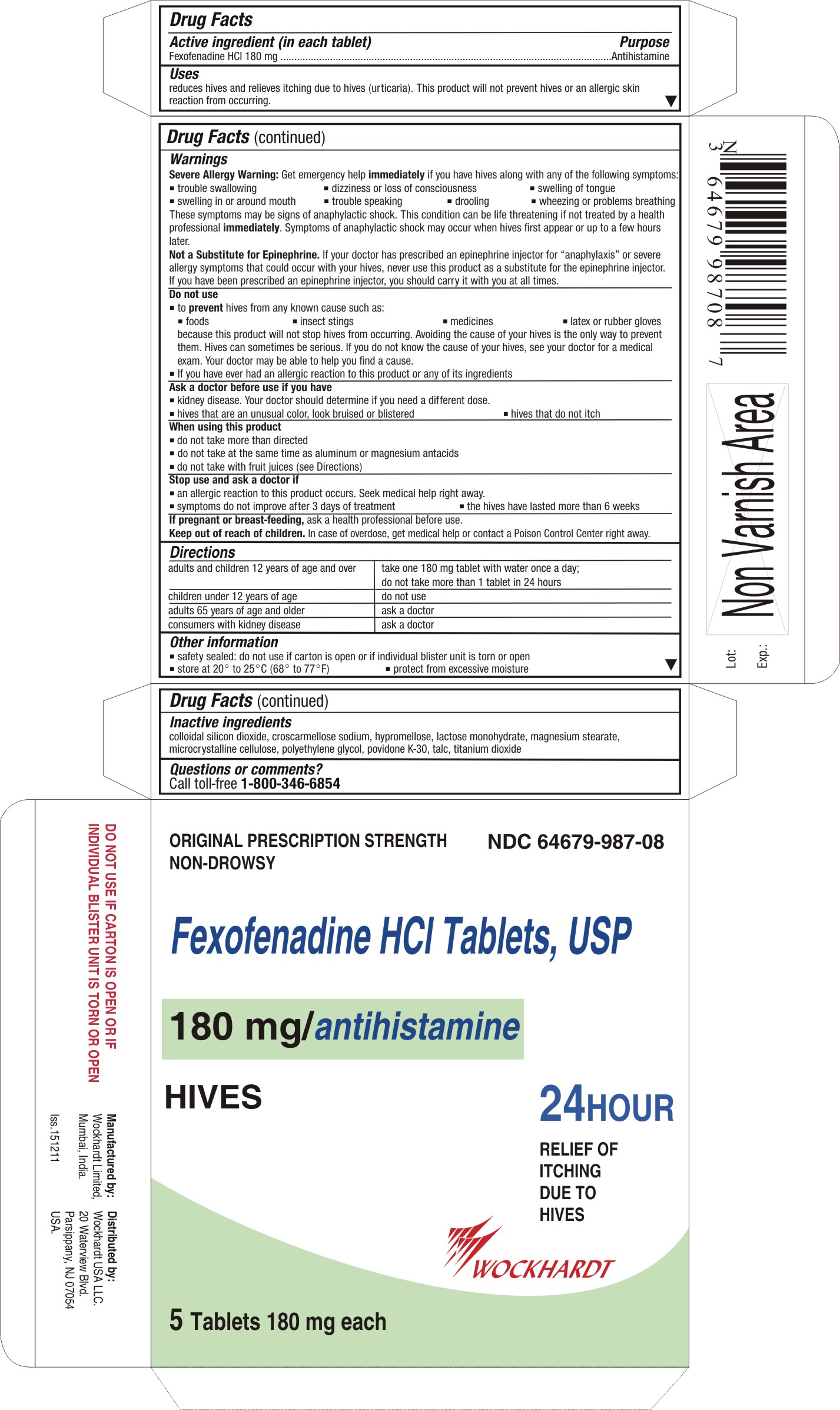 DRUG LABEL: Fexofenadine
NDC: 64679-744 | Form: TABLET, FILM COATED
Manufacturer: Wockhardt USA LLC.
Category: otc | Type: HUMAN OTC DRUG LABEL
Date: 20120305

ACTIVE INGREDIENTS: FEXOFENADINE HYDROCHLORIDE 30 mg/1 1
INACTIVE INGREDIENTS: CELLULOSE, MICROCRYSTALLINE; CROSCARMELLOSE SODIUM; HYPROMELLOSES; LACTOSE MONOHYDRATE; MAGNESIUM STEARATE; POLYETHYLENE GLYCOL; POVIDONE K30; SILICON DIOXIDE; TALC; TITANIUM DIOXIDE

Fexofenadine Tablets

Active ingredient (in each tablet)

For 30 mg:

Fexofenadine HCl 30 mg

For 60 mg:

Fexofenadine HCl 60 mg

For 180 mg:

Fexofenadine HCl 180 mg

Purpose

Antihistamine

Uses

reduces hives and relieves itching due to hives (urticaria). This product will not prevent hives or an allergic skin reaction from occurring.

Warnings

Severe Allergy Warning: Get emergency help immediately if you have hives along with any of the following symptoms:

- trouble swallowing
- dizziness or loss of consciousness
- swelling of tongue
- swelling in or around mouth
- trouble speaking
- drooling
- wheezing or problems breathing

These symptoms may be signs of anaphylactic shock. This condition can be life threatening if not treated by a health professional immediately. Symptoms of anaphylactic shock may occur when hives first appear or up to a few hours later.

Not a Substitute for Epinephrine. If your doctor has prescribed an epinephrine injector for "anaphylaxis" or severe allergy symptoms that could occur with your hives, never use this product as a substitute for the epinephrine injector. If you have been prescribed an epinephrine injector, you should carry it with you at all times.

Do not use

● to prevent hives from any known cause such as:

- foods
- insect stings
- medicines
- latex or rubber gloves because this product will not stop hives from occurring. Avoiding the cause of your hives is the only way to prevent them. Hives can sometimes be serious. If you do not know the cause of your hives, see your doctor for a medical exam. Your doctor may be able to help you find a cause.

● If you have ever had an allergic reaction to this product or any of its ingredients

Ask a doctor before use if you have

- kidney disease. Your doctor should determine if you need a different dose.
- hives that are an unusual color, look bruised or blistered
- hives that do not itch

When using this product

- do not take more than directed
- do not take at the same time as aluminum or magnesium antacids
- do not take with fruit juices (see Directions)

Stop use and ask a doctor if

- an allergic reaction to this product occurs. Seek medical help right away.
- symptoms do not improve after 3 days of treatment
- the hives have lasted more than 6 weeks

If pregnant or breast-feeding

ask a health professional before use.

Keep out of reach of children

In case of overdose, get medical help or contact a Poison Control Center right away.

Directions

For 30 mg:

adults and children 12 years of age and over | take two 30 mg tablets with water every 12 hours; do not take more than 4 tablets in 24 hours
children 6 to under 12 years of age | take one 30 mg tablet with water every 12 hours; do not take more than 2 tablets in 24 hours
children under 6 years of age | do not use
adults 65 years of age and older | ask a doctor
consumers with kidney disease | ask a doctor

For 60 mg:

adults and children 12 years of age and over | take one 60 mg tablet with water every 12 hours; do not take more than 2 tablets in 24 hours
children under 12 years of age | do not use
adults 65 years of age and older | ask a doctor
consumers with kidney disease | ask a doctor

For 180 mg:

adults and children 12 years of age and over | take one 180 mg tablet with water once a day; do not take more than 1 tablet in 24 hours
children under 12 years of age | do not use
adults 65 years of age and older | ask a doctor
consumers with kidney disease | ask a doctor

Other information

- safety sealed: do not use if carton is open or if individual blister unit is torn or open
- store between 20° to 25°C (68° to 77°F)
- protect from excessive moisture

Inactive ingredients

colloidal silicon dioxide, croscarmellose sodium, hypromellose, lactose monohydrate, magnesium stearate, microcrystalline cellulose, polyethylene glycol, povidone K-30, talc, titanium dioxide

Questions or comments?

Call toll-free 1-800-346-6854